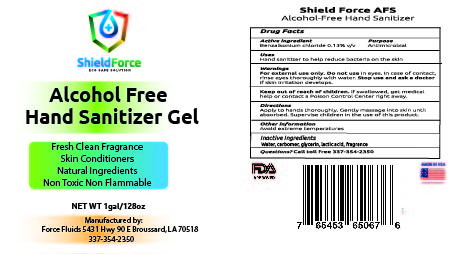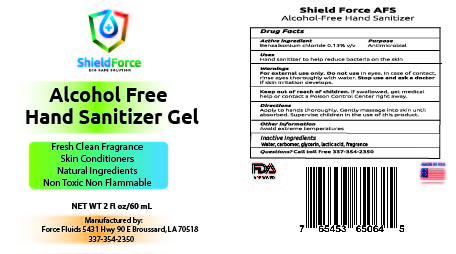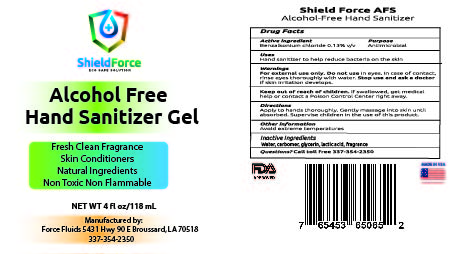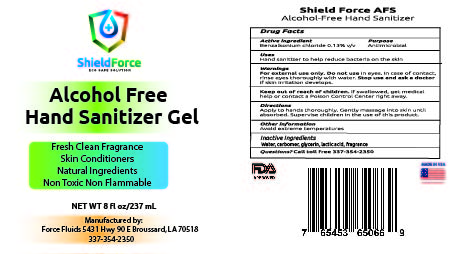 DRUG LABEL: ShieldForce AFS Gel
NDC: 80743-120 | Form: GEL
Manufacturer: Force Fluids LLC
Category: otc | Type: HUMAN OTC DRUG LABEL
Date: 20201119

ACTIVE INGREDIENTS: BENZALKONIUM 1 g/100 mL
INACTIVE INGREDIENTS: GLYCERIN 1.45 mL/100 mL; WATER; LACTIC ACID; FRAGRANCE CLEAN ORC0600327; FRAGRANCE ORANGE ORC2000765

This is a hand sanitizer manufactured according to the Temporary Policy for Preparation of Certain Alcohol-Based Hand Sanitizer Products During the Public Health Emergency (CoViD-19); Guidance for Industry.

The hand sanitizer is manufactured using only the following United States Pharmacopoeia (USP) grade ingredients in the preparation of the product (percentage in final product formulation) consistent with World Health Organization (WHO) recommendations:

1. Benzalklonium Chloride (.11% v/v)
2. Glycerin (.64% v/v).
3. Lactic Acid (3% v/v)
4. Sterile distilled water or boiled cold water.
5. Carbopol (.2% v/v)
6. Fragrance (.75% v/v)

The firm does not add other active or inactive ingredients. Different or additional ingredients may impact the quality and potency of the product.

Active Ingredient(s)

Benzalklonium Chloride .11% v/v. Purpose: Antiseptic

Purpose

Antiseptic, Hand Sanitizer

Use

Hand Sanitizer to help reduce bacteria that potentially can cause disease. For use when soap and water are not available.

Warnings

For external use only. Non flammable.

Do not use

- in children less than 2 months of age
- on open skin wounds

When using this product keep out of eyes, ears, and mouth. In case of contact with eyes, rinse eyes thoroughly with water.
Stop use and ask a doctor if irritation or rash occurs. These may be signs of a serious condition.
Keep out of reach of children. If swallowed, get medical help or contact a Poison Control Center right away.

Stop use and ask a doctor if irritation or rash occurs. These may be signs of a serious condition.

Keep out of reach of children. If swallowed, get medical help or contact a Poison Control Center right away.

Directions

- Place enough product on hands to cover all surfaces. Rub hands together until dry.
- Supervise children under 6 years of age when using this product to avoid swallowing.

Other information

- Store between 15-30C (59-86F)
- Avoid freezing and excessive heat above 40C (104F)

Inactive ingredients

glycerin, carbopol, lactic acid, fragrance, purified water USP

Package Label - Principal Display Panel

AFS Gel 2oz NDC: 80743-120-02

AFS Gel 4oz NDC: 80743-120-04

AFS Gel 8oz NDC: 80743-120-08

AFS Gel 1gal NDC: 80743-120-17